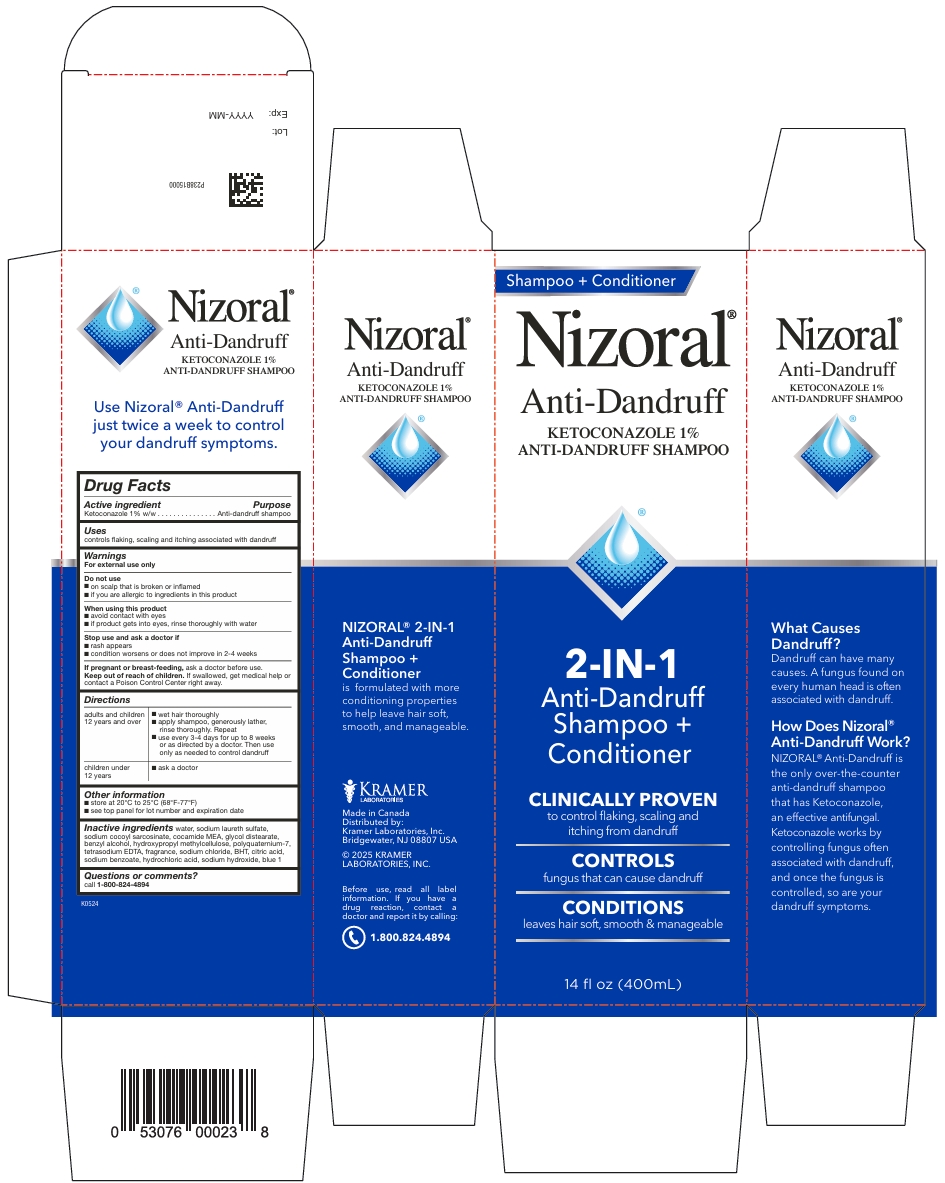 DRUG LABEL: Nizoral
NDC: 55505-233 | Form: SHAMPOO
Manufacturer: Kramer Laboratories
Category: otc | Type: HUMAN OTC DRUG LABEL
Date: 20250821

ACTIVE INGREDIENTS: Ketoconazole 10 mg/1 mL
INACTIVE INGREDIENTS: Benzyl Alcohol; Butylated Hydroxytoluene; Fd&C Blue No. 1; Citric Acid Monohydrate; Coco Monoethanolamide; Glycol Distearate; Hydrochloric Acid; Hypromellose, Unspecified; Polyquaternium-7 (70/30 Acrylamide/Dadmac; 1600000 Mw); Sodium Chloride; Sodium Cocoyl Sarcosinate; Sodium Hydroxide; Sodium Laureth-3 Sulfate; Edetate Sodium; Water; Sodium Benzoate

Drug Facts

ACTIVE INGREDIENT

Active ingredient | Purpose
Ketoconazole 1% w/w | Anti-dandruff shampoo

Uses
controls flaking, scaling and itching associated with dandruff

Warnings
For external use only

Do not use

- on scalp that is broken or inflamed
- if you are allergic to ingredients in this product

When using this product

- avoid contact with eyes
- if product gets into eyes, rinse thoroughly with water

Stop use and ask a doctor if

- rash appears
- condition worsens or does not improve in 2-4 weeks

PREGNANCY OR BREAST FEEDING

If pregnant or breast-feeding, ask a doctor before use.

KEEP OUT OF REACH OF CHILDREN

Keep out of the reach of children. If swallowed, get medical help or
contact a Poison Control Center right away.

Directions

adults and children 12 years and over | - wet hair thoroughly - apply shampoo, generously lather, rinse thoroughly. Repeat - use every 3-4 days for up to 8 weeks or as directed by a doctor. Then use only as needed to control dandruff
children under 12 years | - ask a doctor

Other information

- store at 20°C to 25°C (68°F-77°F)
- see top panel for lot number and expiration date

Inactive ingredients

water, sodium laureth sulfate, sodium cocoyl sarcosinate, cocamide MEA, glycol distearate, benzyl alcohol, hydroxypropyl methylcellulose, polyquaternium-7, tetrasodium EDTA, fragrance, sodium chloride, BHT, citric acid, sodium benzoate, hydrochloric acid, sodium hydroxide, blue 1

Questions or comments?

call 1-800-824-4894

PRINCIPAL DISPLAY PANEL

Shampoo + conditioner
Nizoral®
Anti-Dandruff
KETOCONAZOLE 1%
ANTI-DANDRUFF SHAMPOO
2-IN-1
Anti Drandruff
Shampoo +
Conditioner
CLINICALLY PROVEN
to control flaking, scaling and
itching from dandruff
CONTROLS
fungus that can cause dandruff
CONDITIONS
leaves hair soft, smooth & manageable
14 fl oz (400mL)
What Causes
Dandruff?
Dandruff can have many
causes. A fungus found on
every human head is often
associated with dandruff.
How Does Nizoral®
Anti-Dandruff Work?
NIZORAL® Anti-Dandruff is
the only over-the-counter
anti-dandruff shampoo
that has Ketoconazole,
an effective antifungal.
Ketoconazole works by
controlling fungus often
associated with dandruff,
and once the fungus is
controlled, so are your
dandruff symptoms.
Nizoral®
Anti-Dandruff
KETOCONAZOLE 1%
ANTI-DANDRUFF SHAMPOO
Nizoral® 2-IN-1
Anti-Dandruff
Shampoo +
Conditioner
is formulated with more
conditioning properties
to help leave hair soft,
smooth, and manageable.
KRAMER
LABORATORIES
Made in Canada
Distributed by:
Kramer Laboratories, Inc.
Bridgewater, NJ 08807 USA
© 2025 KRAMER
LABORATORIES, INC.
Before use, read all label
information. If you have a
drug reaction, contact a
doctor and report it by calling:
1.800.824.4894
P238B15000
Lot:
Exp: YYYY-MM
K0524